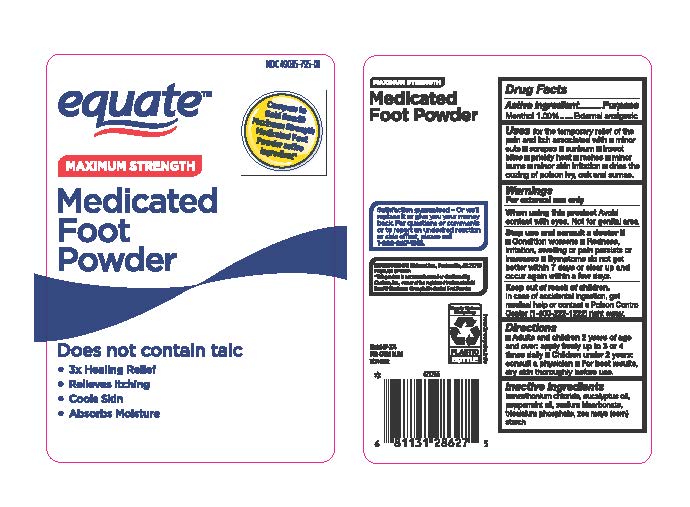 DRUG LABEL: Maximum Strength Medicated Foot Powder
NDC: 49035-795 | Form: POWDER
Manufacturer: Walmart Stores Inc
Category: otc | Type: HUMAN OTC DRUG LABEL
Date: 20251227

ACTIVE INGREDIENTS: MENTHOL 0.1 g/1 g
INACTIVE INGREDIENTS: BENZETHONIUM CHLORIDE; EUCALYPTUS OIL; TRICALCIUM PHOSPHATE; PEPPERMINT OIL; SODIUM BICARBONATE; ZEA MAYS WHOLE

Equate Medicated Foot Powder Menthol 1%

Active ingredient

Menthol 1.0%

Purpose

External analgesic

Use

for the temporary relief of pain and itching associated with

-minor cuts

-scrapes

-sunburn

-insect bites

-prickly heat

-rashes

-minor burns

-minor skin irritation

-dries the oozing of poison ivy, oak and sumac.

Warnings

For external use only.

When using this product

- avoid contact with eyes. Not for genital area

Stop and consult a doctor if

- conditions worsens
- redness, irritation, swelling or pain persist or increases
- symptoms do not get better within 7 days or clear up and occur again within a few days

Keep out of reach of children.

In case of accidental ingestion, get medical help or contact a Poison Control Center (1-800-222-1222) right away.

Directions

- adults and children 2 years of age and over: apply freely up to 3 or 4 times daily
- children under 2 years: consult a physician
- For best results, dry skin thoroughly before use.

Inactive ingredients

benzethonium chloride, eucalyptus oil, peppermint oil, sodium bicarbonate, tricalcium phosphate, Zea mays (corn) starch